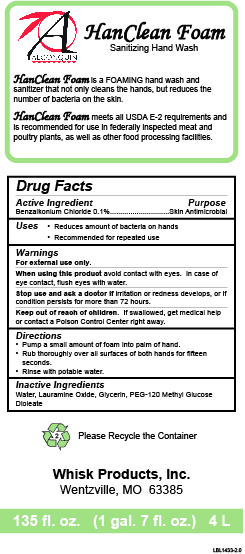 DRUG LABEL: Algonquin HanClean Foam
NDC: 65585-520 | Form: SOAP
Manufacturer: Whisk Products, Inc.
Category: otc | Type: HUMAN OTC DRUG LABEL
Date: 20250609

ACTIVE INGREDIENTS: BENZALKONIUM CHLORIDE 1 mg/1 mL
INACTIVE INGREDIENTS: WATER; LAURAMINE OXIDE; GLYCERIN; PEG-120 METHYL GLUCOSE DIOLEATE

Algonquin HanClean Foam

Active Ingredient

Benzalkonium Chloride 0.1%

Purpose

Skin Antimicrobial

Uses

- Reduces amount of bacteria on hands
- Recommended for repeated use

Warnings

For external use only.

When using this product avoid contact with eyes. In case of eye contact, flush eyes with water.

Stop use and ask a doctor ifirritation or redness develops, or if condition persists for more than 72 hours.

Keep out of reach of children. If swallowed, get medical help or contact a Poison Control Center right away.

Directions

- Pump a small amount of foam into palm of hand.
- Rub thoroughly over all surfaces of both hands for fifteen seconds.
- Rinse with potable water.

Inactive Ingredients

Water, Lauramine Oxide, Glycerin, PEG-120 Methyl Glucose Dioleate